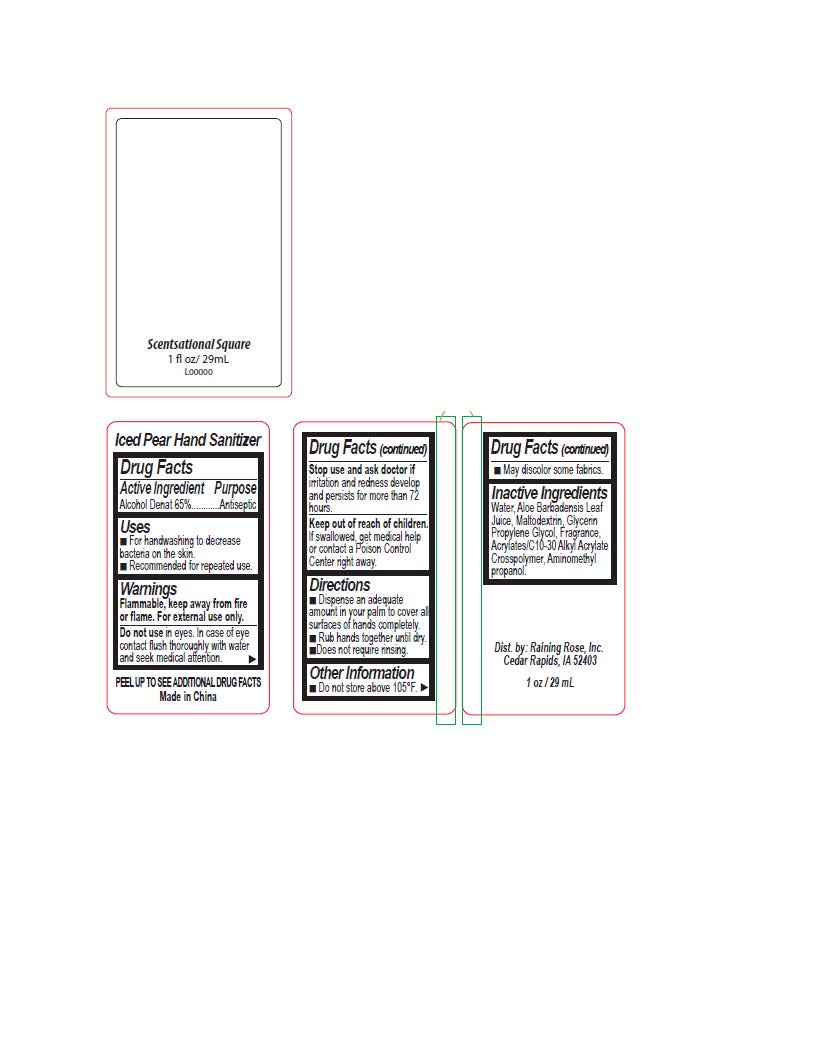 DRUG LABEL: Scentsational Square Hand Sanitizer
NDC: 65692-2079 | Form: GEL
Manufacturer: Raining Rose
Category: otc | Type: HUMAN OTC DRUG LABEL
Date: 20240417

ACTIVE INGREDIENTS: ALCOHOL 65 mL/100 mL
INACTIVE INGREDIENTS: WATER; GLYCERIN; ALOE VERA LEAF; PROPYLENE GLYCOL; CARBOMER INTERPOLYMER TYPE A (55000 CPS); MALTODEXTRIN; AMINOMETHYL PROPANEDIOL

ACTIVE INGREDIENT

Alcohol Denat 65%

PURPOSE

Antiseptic

INDICATIONS AND USAGE

For handwashing to decrease becteria on the skin. Recommended for repeated use.

WARNINGS

Flammable, keep away from fire or flame. For external use only. Do not use in eyes. In case of eye contact flush thoroughly with water and seek medical attention. Stop use and ask doctor if irritation adn redness develop and persists for more than 72 hours.

Keep out of reach of children. If swallowed, get medical help or contact a Poison Control Center right away.

DOSAGE AND ADMINISTRATION

Dispense an adequate amount in your palm to cover all surfaces of hands completely. Rub hands together until dry. Does not require rinsing.

INACTIVE INGREDIENT

Water, Aloe Barbadensis Leaf Juice, Maltodextrin, Glycerin, Propylene Glycol, Fragrance, Acrylates/C10-30 Alkyl Acrylate Crosspolymer, aminomethyl propanol.